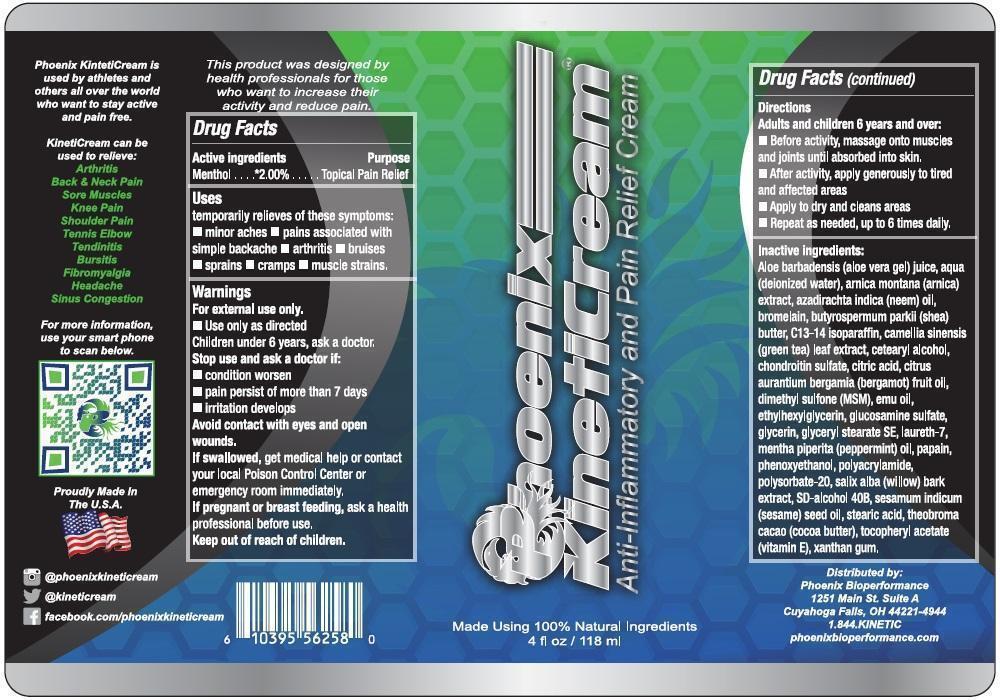 DRUG LABEL: Phoenix KinetiCream Anti-inflammatory and Pain Relief
NDC: 65121-032 | Form: CREAM
Manufacturer: Pure Source, LLC
Category: otc | Type: HUMAN OTC DRUG LABEL
Date: 20231105

ACTIVE INGREDIENTS: MENTHOL 20 mg/1 mL
INACTIVE INGREDIENTS: ALOE VERA LEAF; WATER; ARNICA MONTANA; BROMELAINS; SHEA BUTTER; C13-14 ISOPARAFFIN; GREEN TEA LEAF; CETOSTEARYL ALCOHOL; CITRIC ACID MONOHYDRATE; BERGAMOT OIL; DIMETHYL SULFONE; EMU OIL; ETHYLHEXYLGLYCERIN; GLUCOSAMINE SULFATE; GLYCERIN; GLYCERYL STEARATE SE; LAURETH-7; PEPPERMINT OIL; PAPAIN; PHENOXYETHANOL; POLYSORBATE 20; WILLOW BARK; SESAME OIL; STEARIC ACID; COCOA BUTTER; .ALPHA.-TOCOPHEROL; XANTHAN GUM

Phoenix KinetiCream Antiflammatory and Pain Relief Cream

Active Ingredients

Menthol 2.00%

Purpose

Topical Pain Relief

Uses

temporary relieves of these symptoms:

- minor aches
- pains associated with simple backache
- arthritis
- bruises
- sprains
- cramps
- muscle strains.

Warnings

For external use only.

- Use only as directed children under 6 years, ask a doctor.

Stop use and ask a doctor if:

- condition worsen
- pain persist of more than 7 days
- irritation develops

Avoid contact with eyes and open wounds.

If swallowed, get medical help or contact your local Poison Control Center or emergency room immediately.

If pregnant or breast feeding

ask a health professional before use.

Directions

Adults and children 6 years and over:

- Before activity, massage onto muscles and joints until absorbed into skin.
- After activity, apply generously to tired and affected areas
- Apply to dry and cleans areas
- Repeat as needed, up to 6 times daily.

Inactive ingredients:

Aloe barbadensis (aloe vera gel) juice, aqua (deionized water), arnica montana (arnica) extract, azadirachta indica (neem) oil, bromelain, butyrospermum parkii (shea) butter, C13-14 isoparaffin, camellia sinensis (green tea) leaf extract, cetearyl alcohol, chondroitin sulfate, citric acid, citrus aurantium bergamia (bergamot) fruit oil, dimethyl sulfone (MSM), emu oil, ethylhexylglycerin, glucosamine sulfate, glycerin, glyceryl stearate SE, laureth-7, mentha piperita (peppermint) oil, papain, phenoxyethanol, polyacrylamide, polysorbate-20, salix alba (willow) bark extract, SD-Alcohol 40B, sesamum indicum (sesame) seed oil, stearic acid, theobroma cacao (cocoa butter), tocopheryl acetate (vitamin E), xanthan gum.